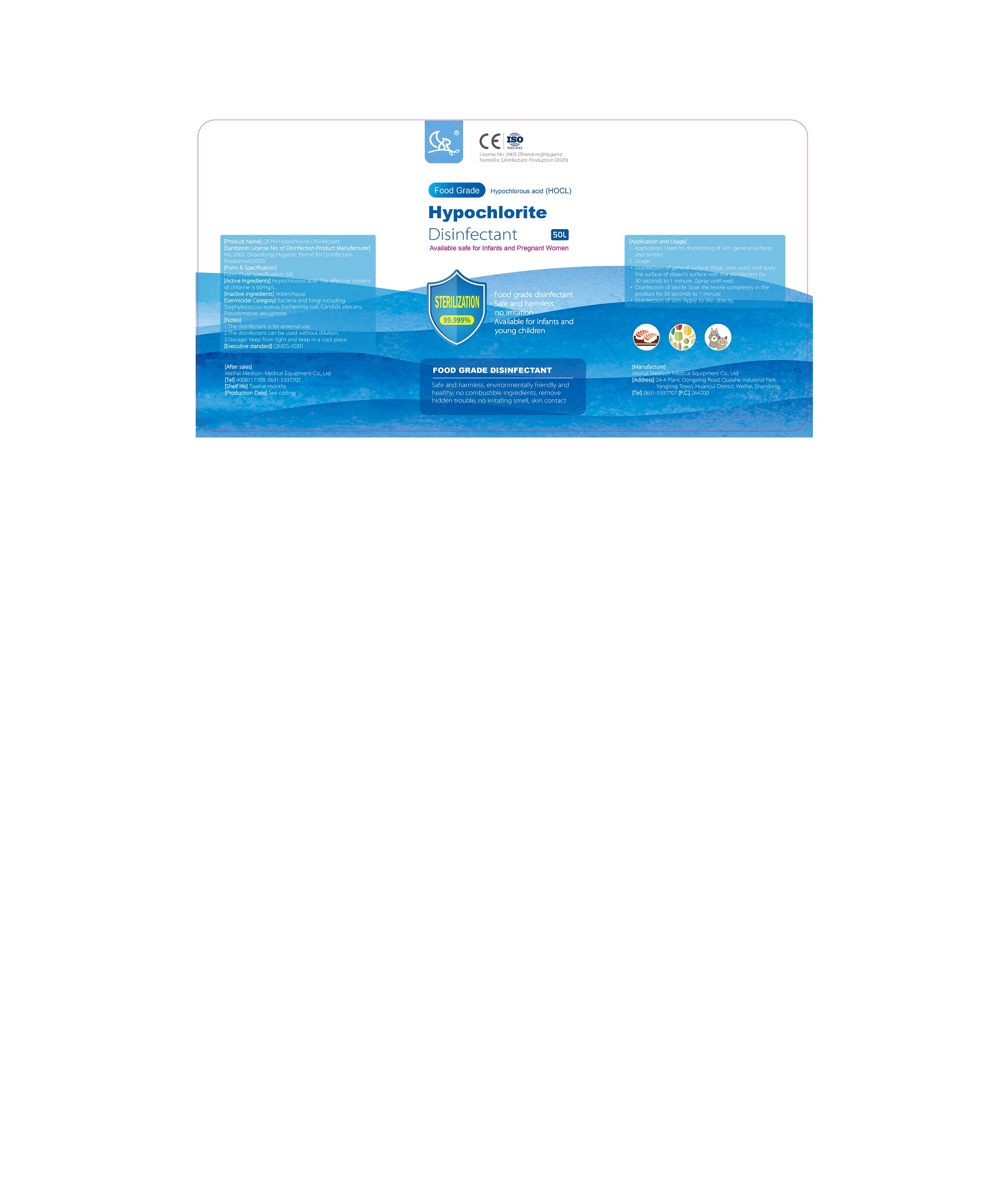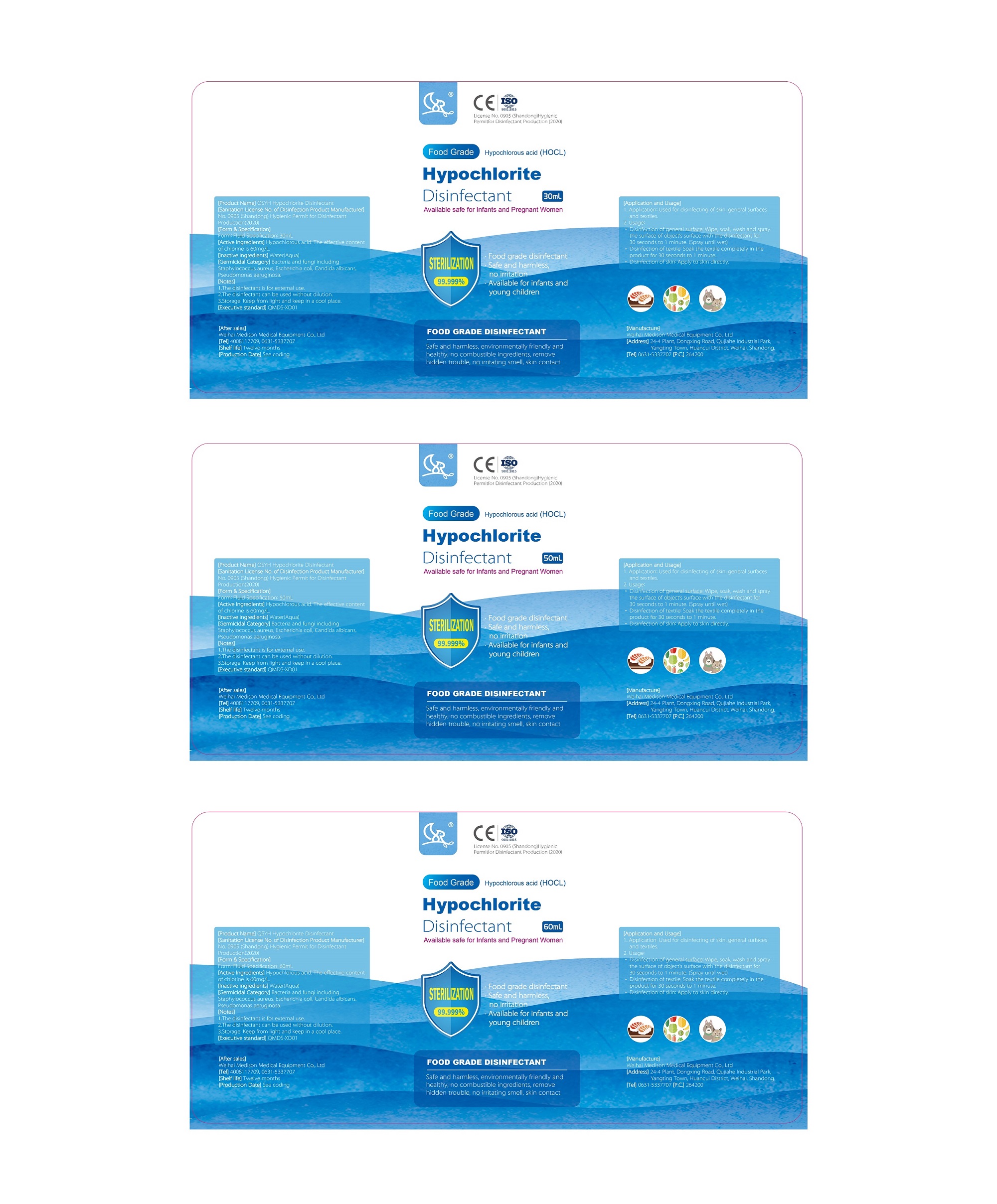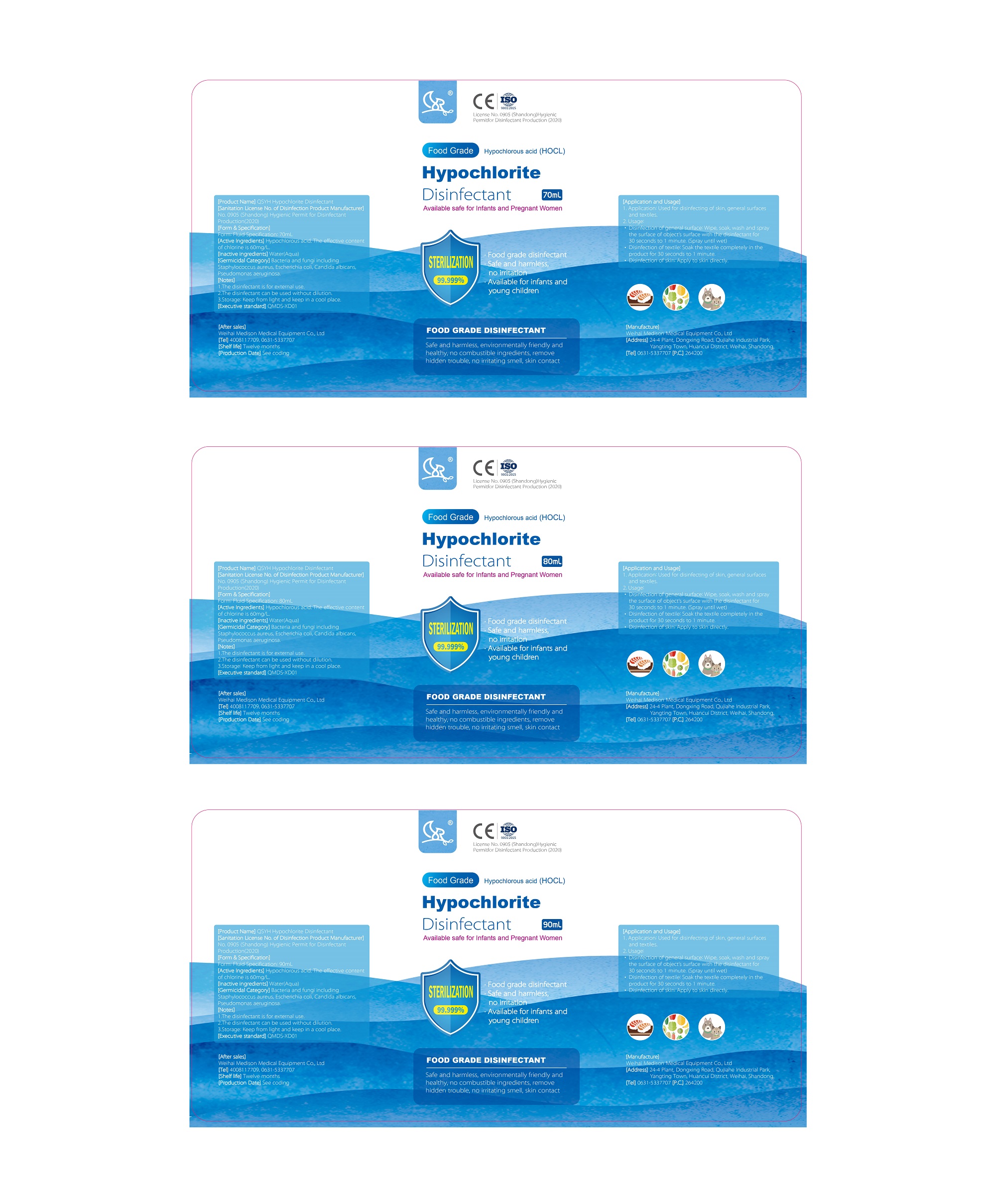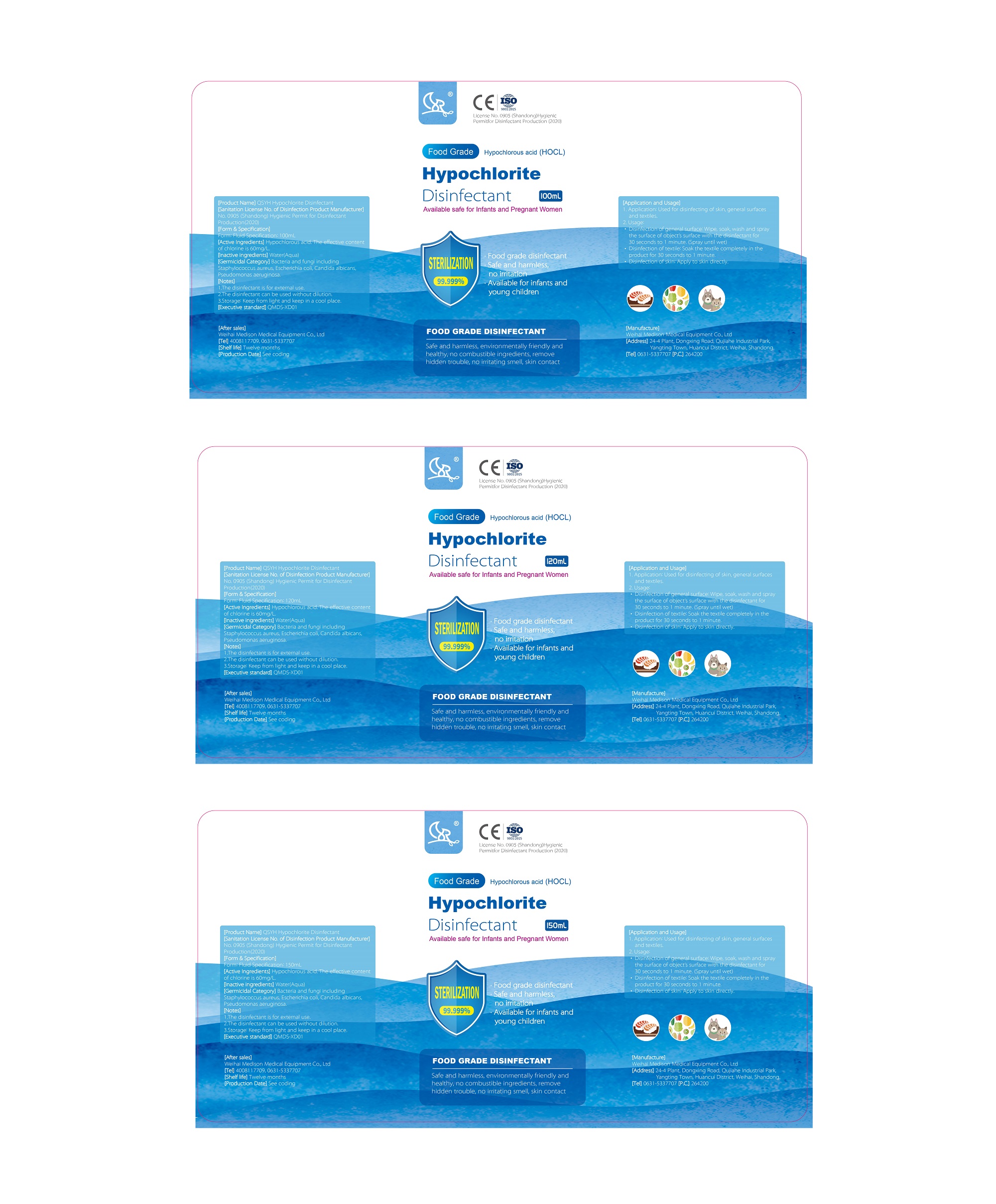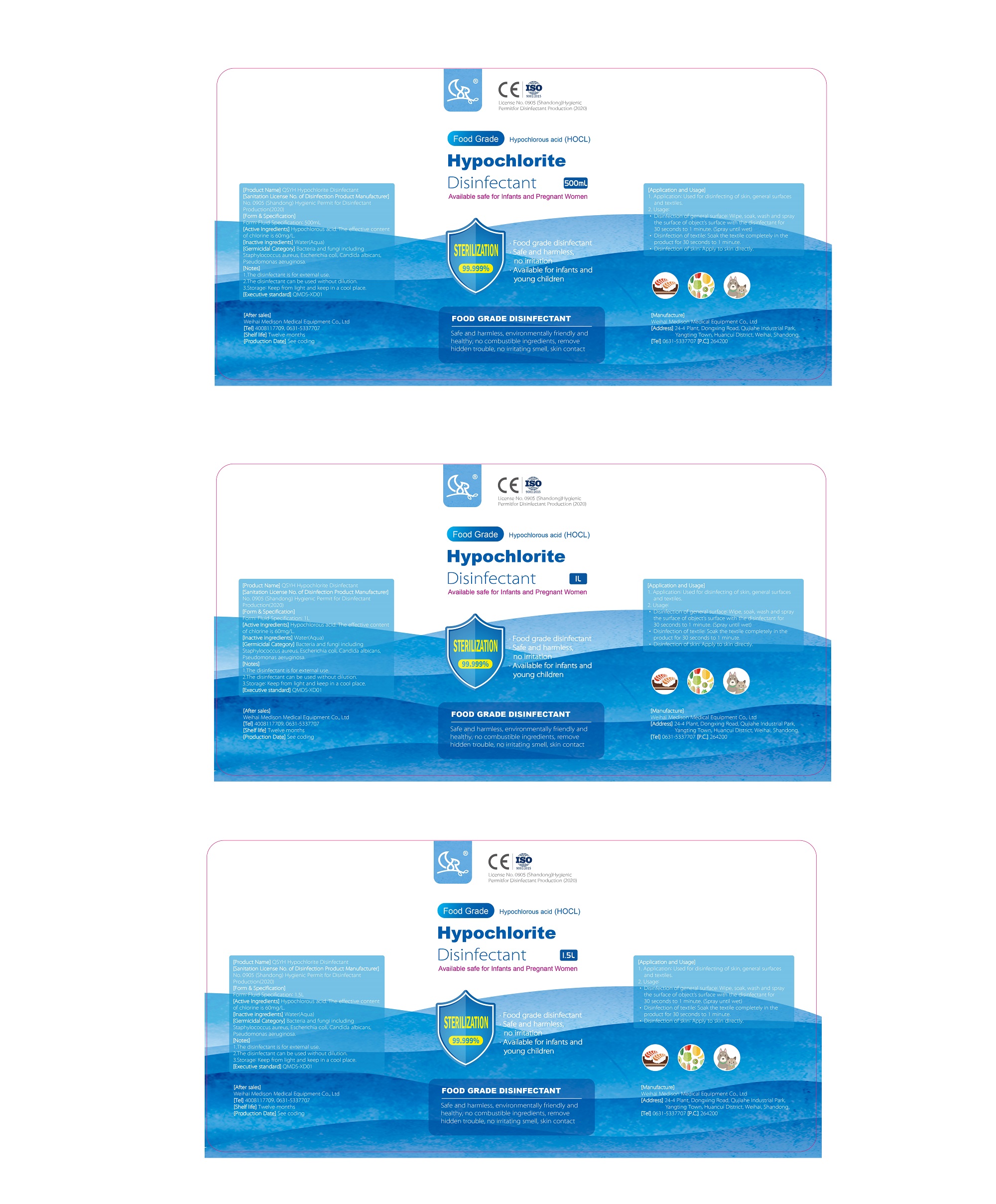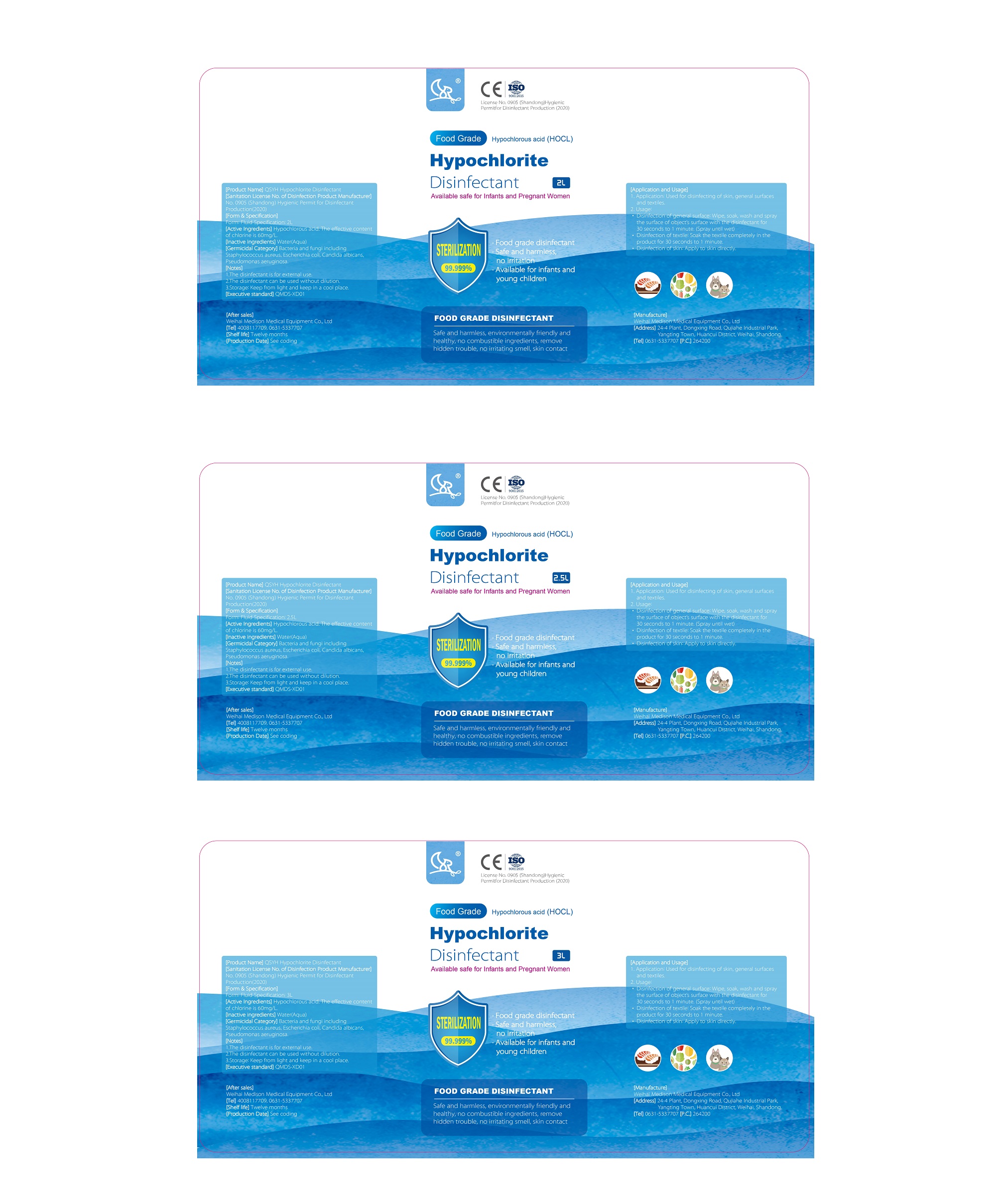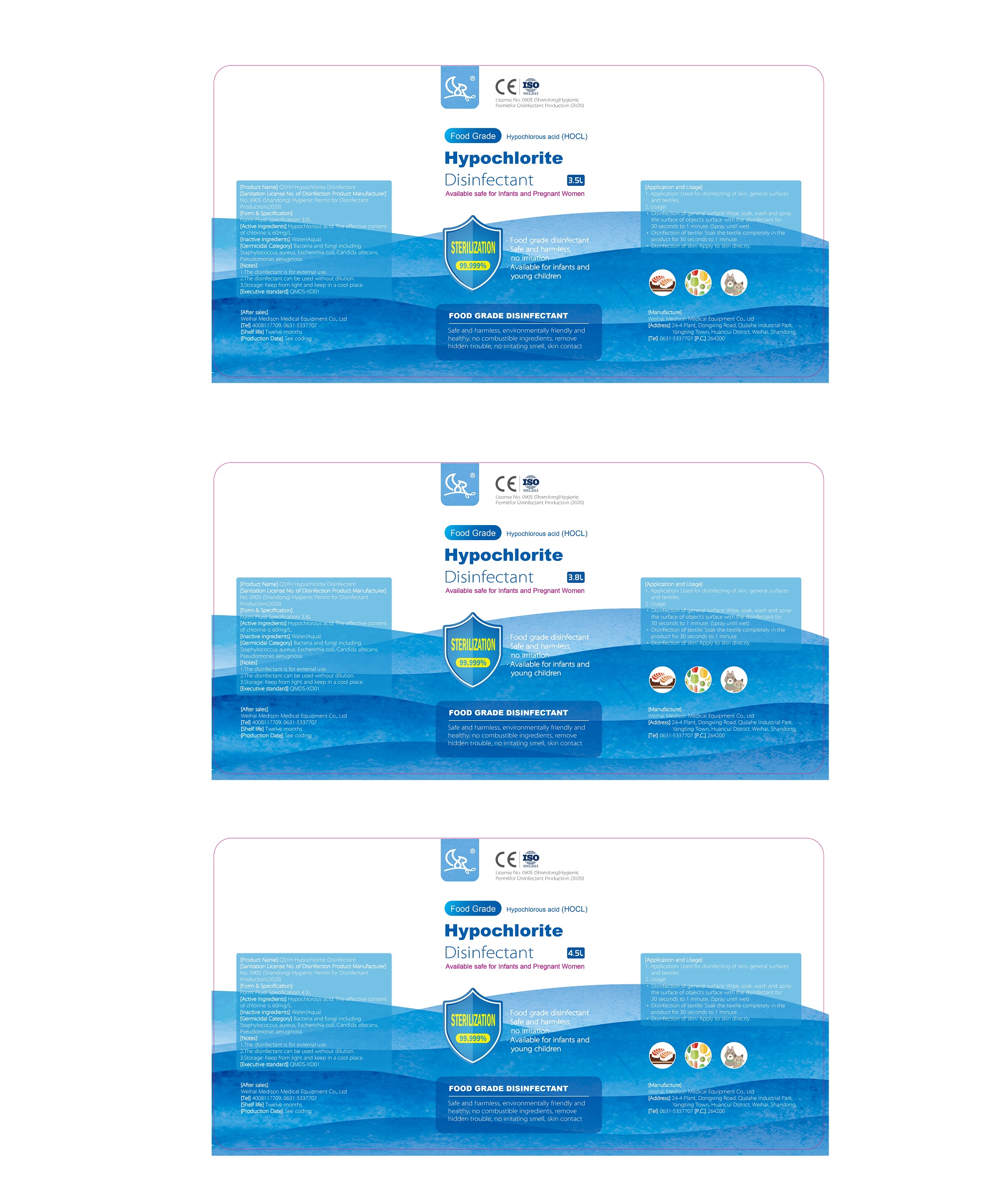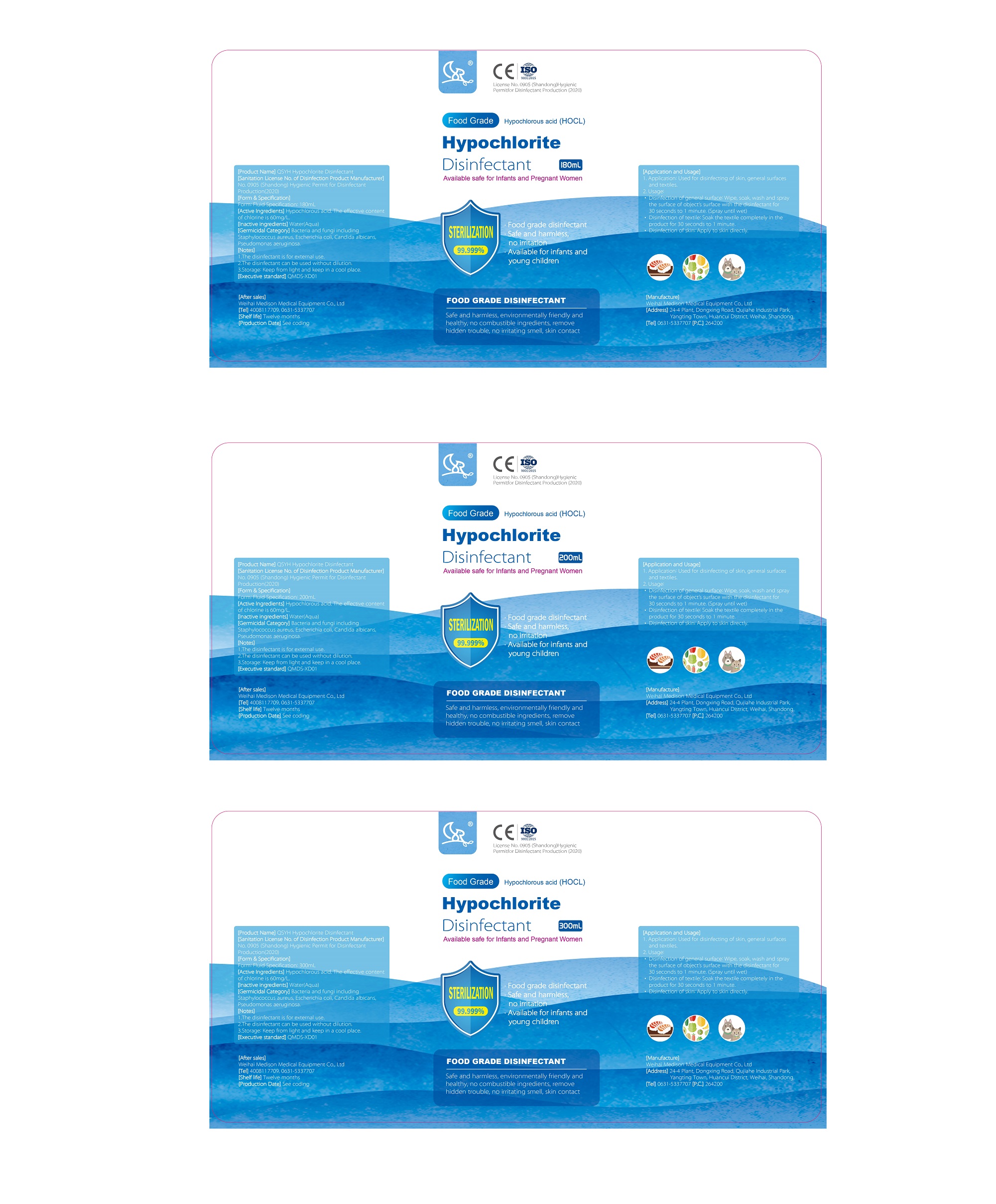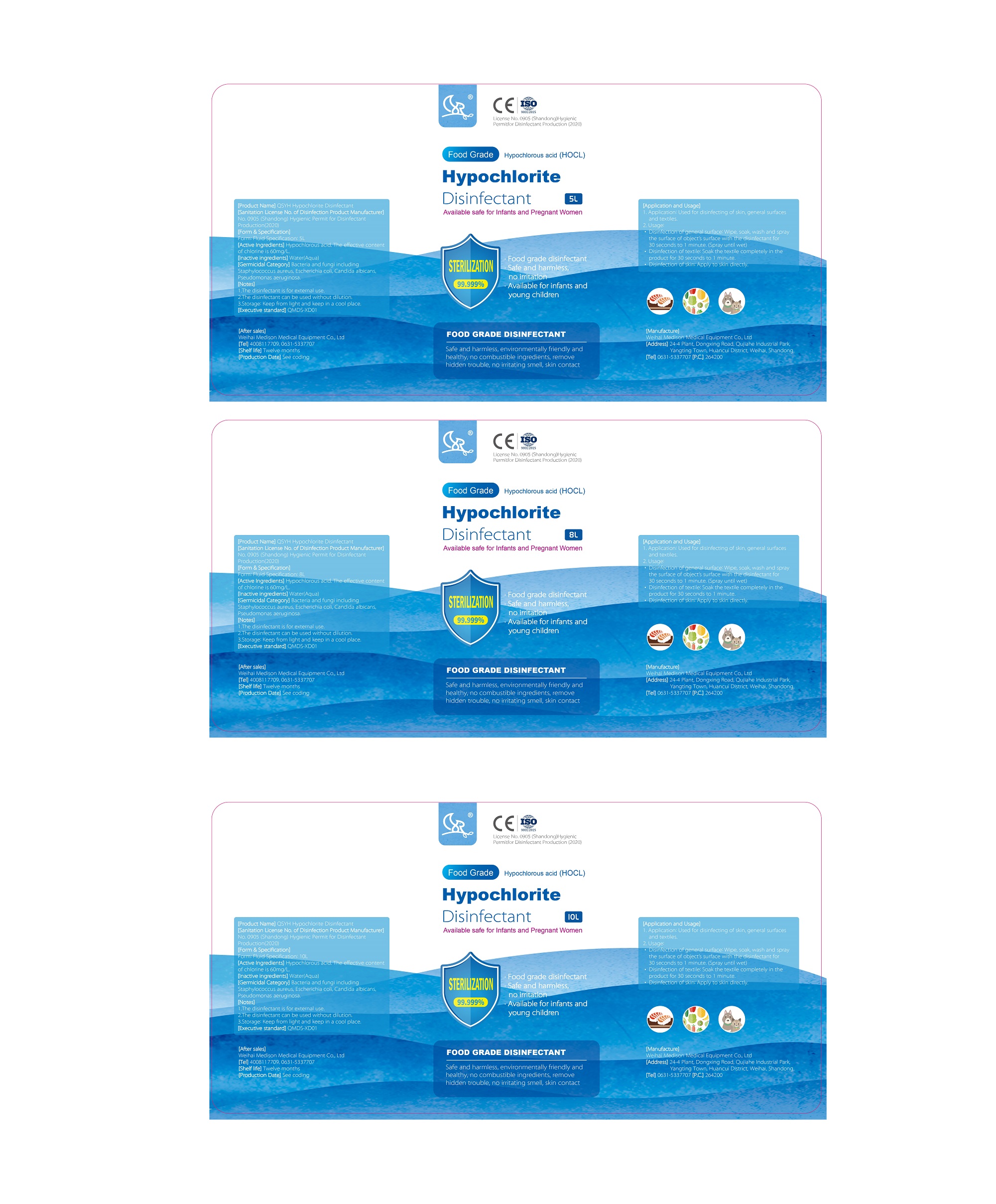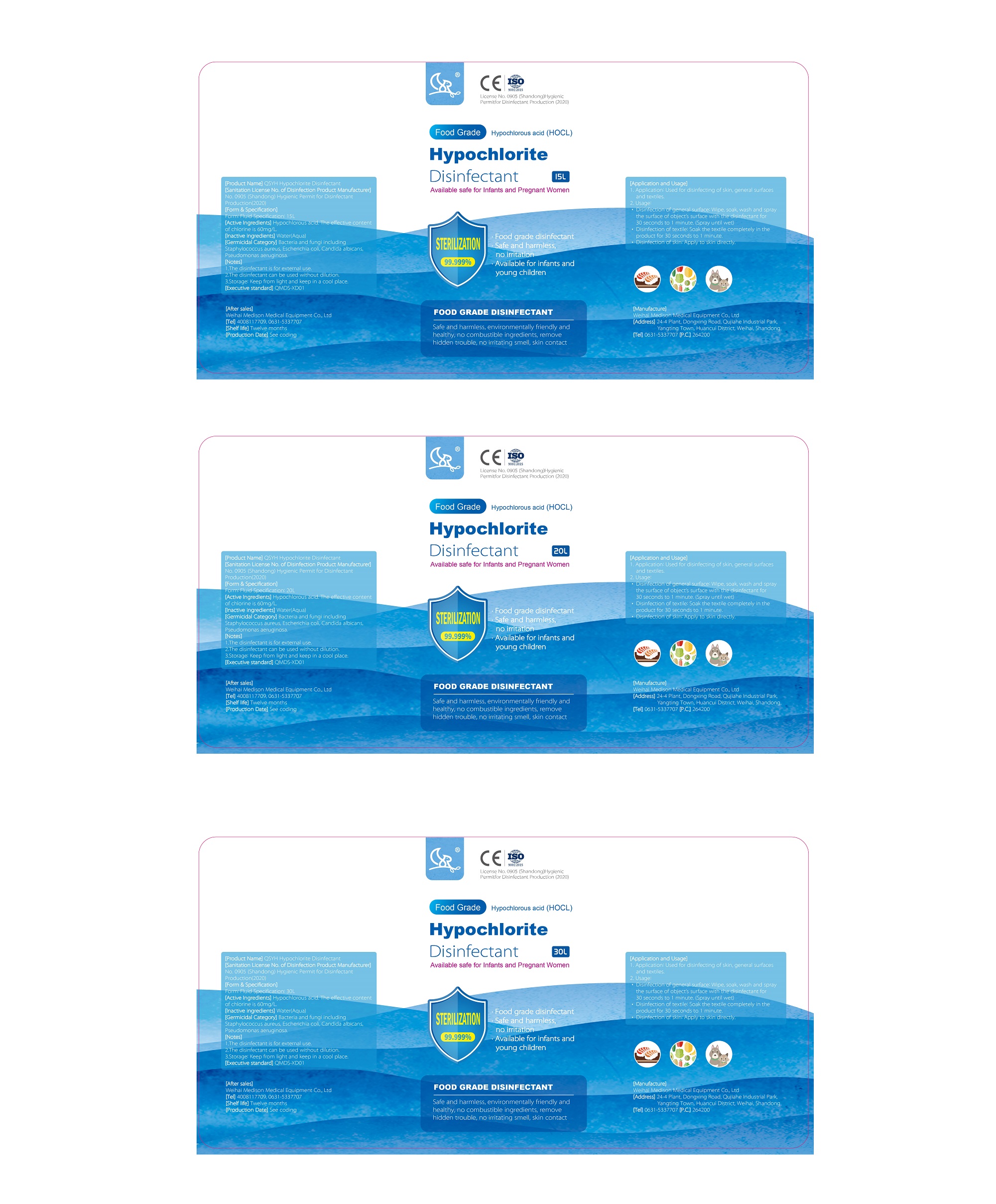 DRUG LABEL: QSYH Hypochlorite Disinfectant
NDC: 74744-005 | Form: LIQUID
Manufacturer: Weihai Medison Medical Equipment Co., Ltd
Category: otc | Type: HUMAN OTC DRUG LABEL
Date: 20231009

ACTIVE INGREDIENTS: HYPOCHLOROUS ACID 0.006 g/100 mL
INACTIVE INGREDIENTS: WATER

QSYH Hypochlorite Disinfectant

FOOD GRADE DISINFECTANT

Safe and harmless, environmentally friendly and healthy, no combustible ingredients, remove hidden trouble, no irritating smell, skin contact

Active Ingredients

Hypochlorous acid. The effective content of chlorine is 60 mg/L

Inactive ingredients

water(Aqua)

Germicida Category

Bacteria and fungi including Staphylococcus aureus, Escherichia coli, Candida albicans, Pseudomonas aeruginosa

Notes

1.The disinfectant is for external use
2.The disinfectant can be used without dilution
3.Storage: Keep from light and keep in a cool place

Application and Used

Application for disinfecting of skin, general surfaces and textiles

Directions

1.Wipe,soak,wash and spray the surface of object's surface with the disinfectant for 30 seconds to 1 minute.(Spray until wet).2.Soak the textile completely in the product for 30 seconds to 1 minute.3.Apply to skin directly.